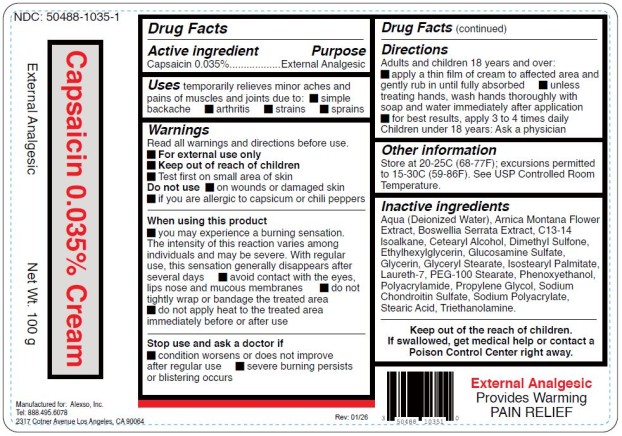 DRUG LABEL: Capsaicin 0.035 Percent
NDC: 50488-1035 | Form: CREAM
Manufacturer: Alexso, Inc
Category: otc | Type: HUMAN OTC DRUG LABEL
Date: 20260213

ACTIVE INGREDIENTS: CAPSAICIN 0.035 g/100 g
INACTIVE INGREDIENTS: WATER; ARNICA MONTANA FLOWER; BOSWELLIA SERRATA WHOLE; CETOSTEARYL ALCOHOL; CHONDROITIN SULFATE (BOVINE); ETHYLHEXYLGLYCERIN; GLUCOSAMINE SULFATE; GLYCERIN; GLYCERYL MONOSTEARATE; C13-14 ISOPARAFFIN; ISOSTEARYL PALMITATE; LAURETH-7; DIMETHYL SULFONE; PEG-100 STEARATE; PHENOXYETHANOL; POLYACRYLAMIDE (10000 MW); PROPYLENE GLYCOL; SODIUM POLYACRYLATE (2500000 MW); STEARIC ACID; TROLAMINE

Capsaicin 0_035 Percent Cream

Drug Facts

Active ingredient

Capsaicin 0.035%

Purpose

External analgesic

Uses

Temporarily relieves minor aches and pains of muscles and joints due to:

• simple backache

• arthritis

• strains

• sprains

Warnings

For external use only

Read all warnings and directions before use. Test first on small area of skin.

Do not use

• On wounds or damaged skin

• If you are allergic to capsicum or chili peppers

When using this product

• You may experience a burning sensation. The intensity of this reaction varies among individuals and may be severe. With regular use, this sensation generally disappears after several days.

• Avoid contact with the eyes, lips, nose and mucous membranes

• Do not tightly wrap or bandage the treated area

• Do not apply heat to the treated area immediately before or after use

Stop use and ask a doctor if

• Condition worsens or does not improve after regular use

• Severe burning persists or blistering occurs

Keep out of reach of children.

If swallowed, get medical help or contact a Poison Control Center immediately.

Directions

Adults and children 18 years of age and older:

Apply a thin film of cream to affected area and gently rub in until fully absorbed unless treating hands. Wash hands thoroughly with soap and water immediately after application for best results. Apply 3 to 4 times daily.

Children under 18 years: Ask a doctor

Other information

Store at room temperature 15°-30°C (59°-86°F)

Inactive ingredients

Aqua (Deionized Water), Arnica Montana Flower Extract, Boswellia Serrata Extract, Cetearyl Alcohol, Chondroitin Sulfate, Ethylhexylglycerin, Glucosamine Sulfate, Glycerin, Glyceryl Stearate, C13-14 Isoparaffin, Isostearyl Palmitate, Laureth-7, Methylsufonylmethane (MSM), PEG-100 Stearate, Phenoxyethanol, Polyacrylamide, Propylene Glycol, Sodium Polyacrylate, Stearic Acid, and Triethanolamine

Principal Display Panel

Capsaicin 0.035% cream
NDC 50488-1035-1
Net Wt. 100 g